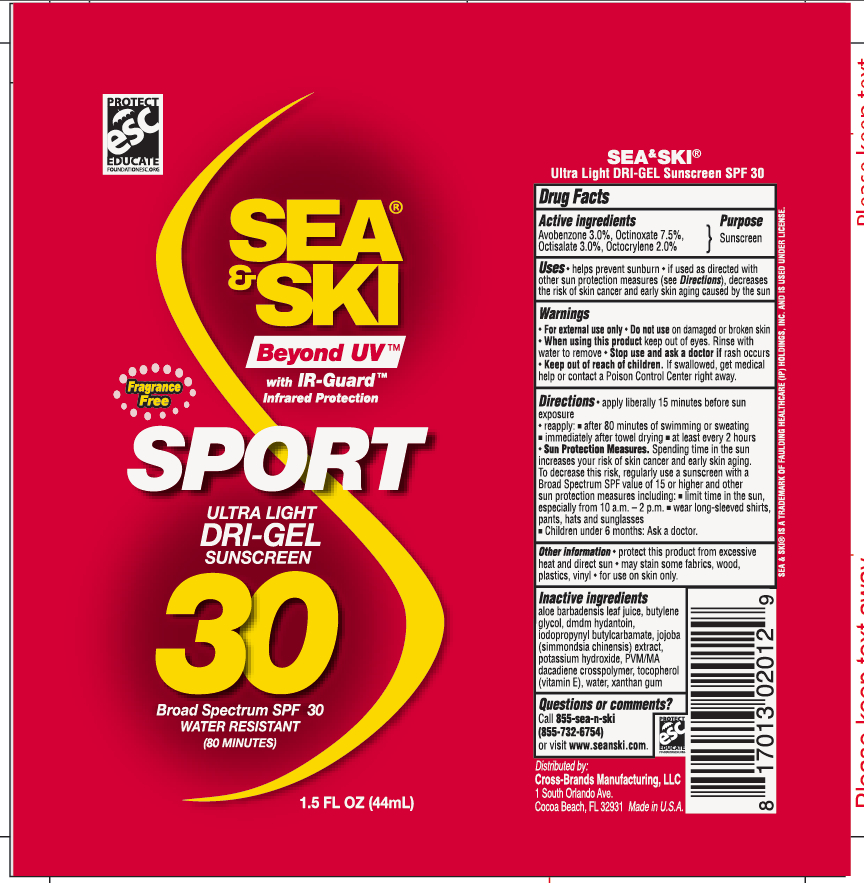 DRUG LABEL: General Protection
NDC: 71153-2012 | Form: GEL
Manufacturer: Cross-Brands Manufacturing LLC
Category: otc | Type: HUMAN OTC DRUG LABEL
Date: 20170226

ACTIVE INGREDIENTS: OCTISALATE 3 g/1 mL; OCTINOXATE 7.5 g/1 mL; AVOBENZONE 3 g/1 mL; OCTOCRYLENE 2 g/1 mL
INACTIVE INGREDIENTS: XANTHAN GUM; ALOE VERA LEAF

Sea & Ski SPF 30 Dry Gel